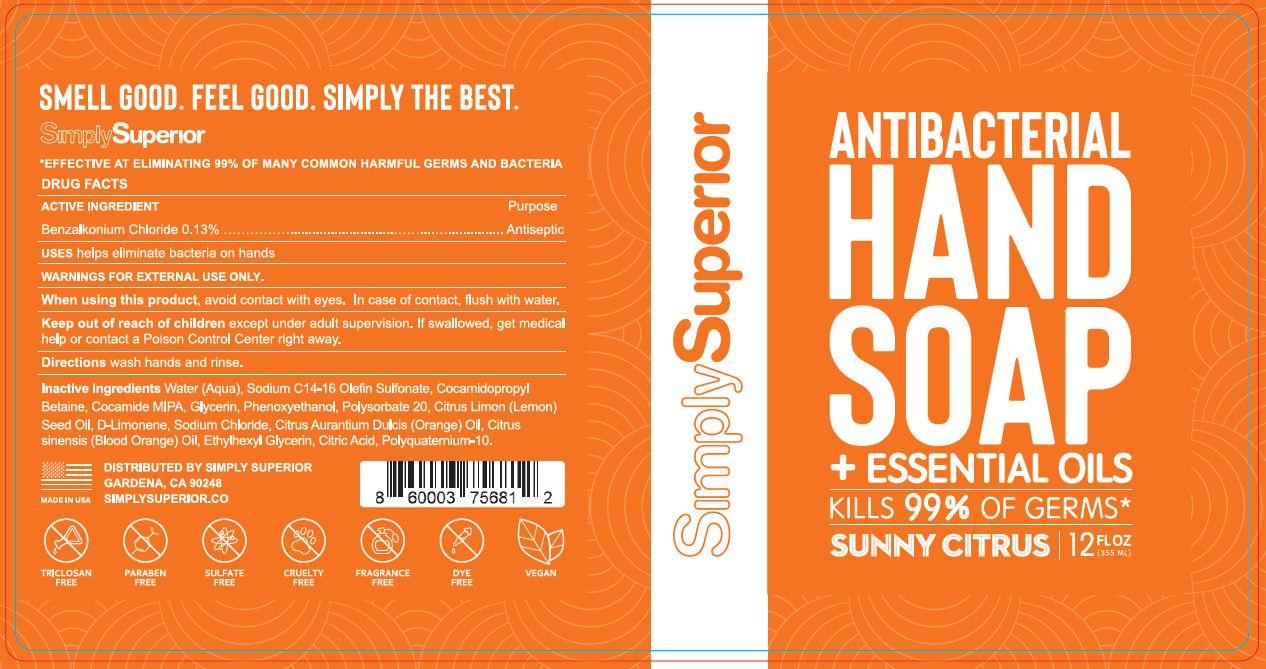 DRUG LABEL: ANTIBACTERIAL HAND
NDC: 50518-309 | Form: SOAP
Manufacturer: CUSTOM RESEARCH LABS INC
Category: otc | Type: HUMAN OTC DRUG LABEL
Date: 20220329

ACTIVE INGREDIENTS: BENZALKONIUM CHLORIDE 0.13 g/100 mL
INACTIVE INGREDIENTS: WATER; SODIUM C14-16 OLEFIN SULFONATE; COCAMIDOPROPYL BETAINE; COCO MONOISOPROPANOLAMIDE; GLYCERIN; PHENOXYETHANOL; POLYSORBATE 20; LEMON OIL; LIMONENE, (+)-; SODIUM CHLORIDE; ORANGE OIL; CITRUS SINENSIS SEED OIL; ETHYLHEXYLGLYCERIN; ANHYDROUS CITRIC ACID; POLYQUATERNIUM-10 (1000 MPA.S AT 2%)

CRL (as CMO) - ANTIBACTERIAL HAND SOAP (50518-309)

ACTIVE INGREDIENT

BENZALKONIUM CHLORIDE 0.13%

PURPOSE

ANTISEPTIC

USES

HELPS ELIMINATE BACTERIA ON HANDS

WARNINGS

FOR EXTERNAL USE ONLY.

WHEN USING THIS PRODUCT, AVOID CONTACT WITH EYES. IN CASE OF CONTACT, FLUSH WITH WATER.

KEEP OUT OF REACH OF CHILDREN EXCEPT UNDER ADULT SUPERVISION. IF SWALLOWED, GET MEDICAL HELP OR CONTACT A POISON CONTROL CENTER RIGHT AWAY.

DIRECTIONS

WASH HANDS AND RINSE.

INACTIVE INGREDIENTS

WATER (AQUA), SODIUM C14-16 OLEFIN SULFONATE, COCAMIDOPROPYL BETAINE, COCAMIDE MIPA, GLYCERIN, PHENOXYETHANOL, POLYSORBATE 20, CITRUS LIMON (LEMON) SEED OIL, D-LIMONENE, SODIUM CHLORIDE, CITRUS AURANTIUM DULCIS (ORANGE) OIL, CITRUS SINENSIS (BLOOD ORANGE) OIL, ETHYLHEXYL GLYCERIN, CITRIC ACID, POLYQUATERNIUM-10.